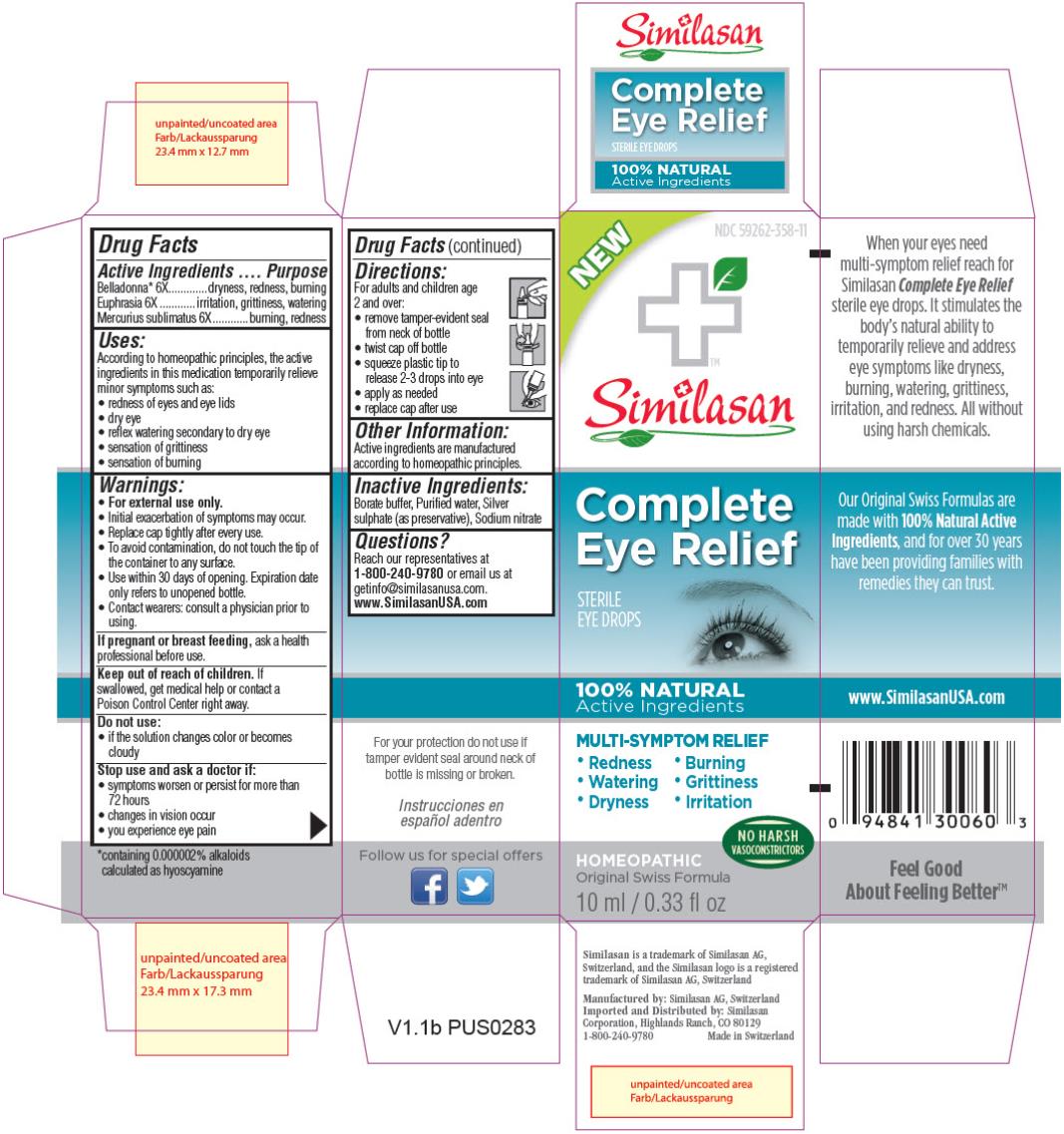 DRUG LABEL: Complete Eye Relief
NDC: 59262-358 | Form: SOLUTION/ DROPS
Manufacturer: Similasan Corporation
Category: homeopathic | Type: HUMAN OTC DRUG LABEL
Date: 20140109

ACTIVE INGREDIENTS: ATROPA BELLADONNA 6 [hp_X]/10 mL; EUPHRASIA STRICTA 6 [hp_X]/10 mL; MERCURIC CHLORIDE 6 [hp_X]/10 mL
INACTIVE INGREDIENTS: BORIC ACID; WATER; SILVER SULFATE; SODIUM NITRATE

Complete Eye Relief
Drug Facts

Active Ingredient

Belladonna* 6X

*containing 0.000002% alkaloids calculated as hyoscyamine

Purpose

dryness, redness, burning

Active Ingredient

Euphrasia 6X

Purpose

irritation, grittiness, watering

Active Ingredient

Mercurius sublimatus 6X

Purpose

burning, redness

Uses:

According to homeopathic principles, the active ingredients in this medication temporarily relieve minor symptoms such as:

- redness of eyes and eye lids
- dry eye
- reflex watering secondary to dry eye
- sensation of grittiness
- sensation of burning

Warnings:

- For external use only.
- Initial exacerbation of symptoms may occur.
- Replace cap tightly after every use.
- To avoid contamination, do not touch the tip of the container to any surface.
- Use within 30 days of opening. Expiration date only refers to unopened bottle.
- Contact wearers: consult a physician prior to using.

If pregnant or breast feeding,

ask a health professional before use.

Keep out of reach of children.

If swallowed, get medical help or contact a Poison Control Center right away.

Do not use:

- if the solution changes color or becomes cloudy

Stop use and ask a doctor if:

- symptoms worsen or persist for more than 72 hours
- changes in vision occur
- you experience eye pain

Directions:

For adults and children age

2 and over:

- remove tamper-evident seal from neck of bottle
- twist cap off bottle
- squeeze plastic tip to release 2-3 drops into eye
- apply as needed
- replace cap after use

Other Information:

Active ingredients are manufactured according to homeopathic principles.

Inactive Ingredients:

Borate buffer, Purified water, Silver sulphate (as preservative), Sodium nitrate

Questions?

Reach our representatives at 1-800-240-9780 or email us at getinfo@similasanusa.com.

www.SimilasanUSA.com

PRINCIPAL DISPLAY PANEL

NEW
NDC 59262-358-11
Similasan
Complete Eye Relief
STERILE EYE DROPS
10 mL/0.33 fl oz